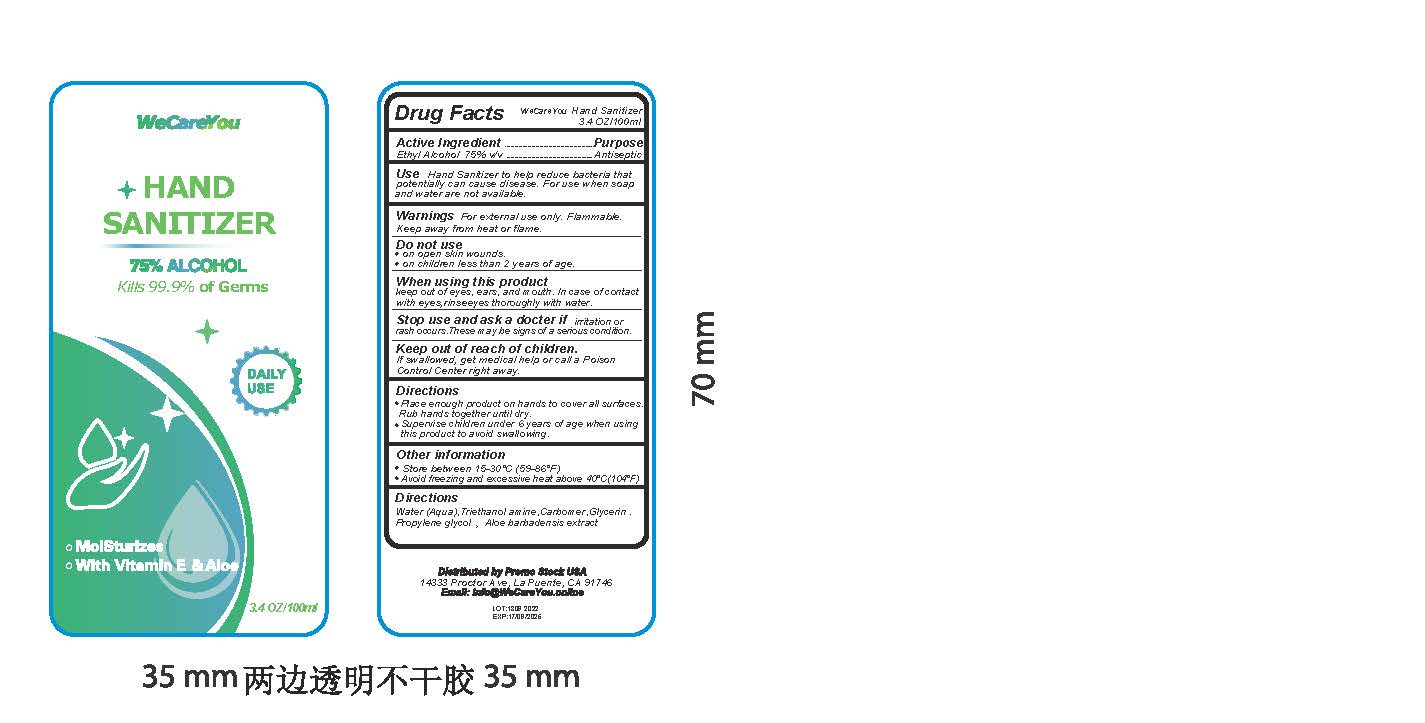 DRUG LABEL: Hand Sanitizer
NDC: 76860-004 | Form: GEL
Manufacturer: Taizhou Huangyuan Liweir Cosmetic Technology Ltd.
Category: otc | Type: HUMAN OTC DRUG LABEL
Date: 20220915

ACTIVE INGREDIENTS: ALCOHOL 75 mL/100 mL
INACTIVE INGREDIENTS: WATER; PROPYLENE GLYCOL; CARBOMER HOMOPOLYMER, UNSPECIFIED TYPE; GLYCERIN; TROLAMINE; ALOE

Hand Sanitizer Gel

Active Ingredient

Ethyl Alcohol 15% v/v

Purpose

Antiseptic

Use

Hand Sanitizer to help reduce bacteria that potentially can caise disease. For use when soap and water are not available.

Warnings

For external use only. Flammable. Keep away from heat or flame.

Do not use

- on open skin wounds

- on children less than 2 years of age.

When using this product

keep out of eyes, ears, and mouth. In case of contact with eyes,rinse eyes thoroughly with water.

Stop use and ask a doctor if

irritation or rash occurs. These may be signs of a serious condition.

Keep out of reach of children.

If swallowed, get medical help or call a Poison Control Center right away.

Directions

- Place enough product on hands to cover all surfaces. Rub hands together until dry.

- Supervise children under 6 years of age when using this product to avoid swallowing.

Other information

- Store between 15-30'C (59-86')

- Avoid freezing and excessive heat above 40'C(104'F)

Directions

Water (Aqua), Thiethanol amine, Carbomer, Glycerin, Propylene glycol, Aloe barbadensis extract